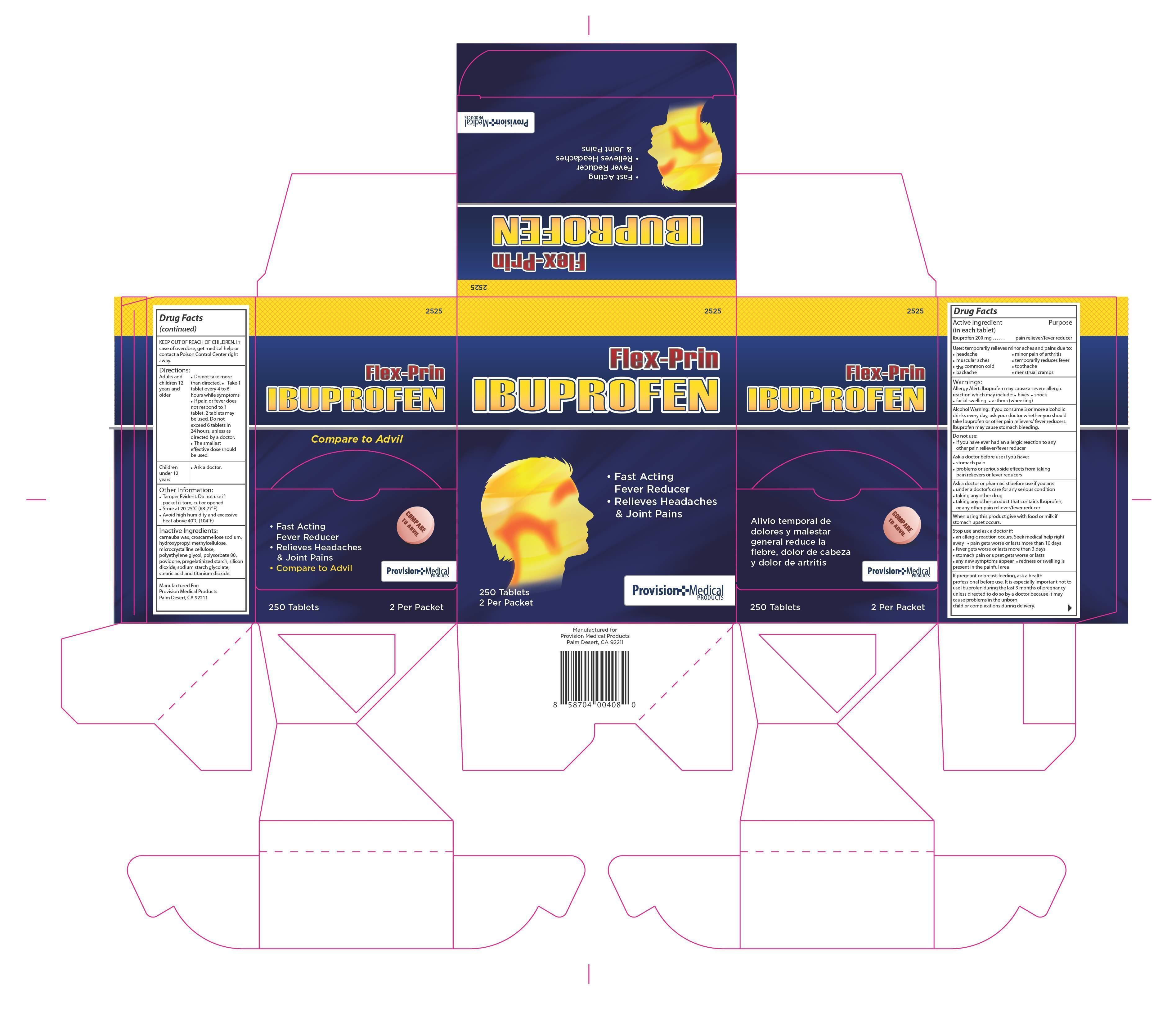 DRUG LABEL: Flex-Prin
NDC: 69103-2525 | Form: TABLET
Manufacturer: Provision Medical Products
Category: otc | Type: HUMAN OTC DRUG LABEL
Date: 20230105

ACTIVE INGREDIENTS: IBUPROFEN 200 mg/1 1
INACTIVE INGREDIENTS: CROSCARMELLOSE SODIUM; CARNAUBA WAX; HYPROMELLOSES; POLYETHYLENE GLYCOL 400; STEARIC ACID; CELLULOSE, MICROCRYSTALLINE; POVIDONE K30; STARCH, PREGELATINIZED CORN; POLYSORBATE 80; SILICON DIOXIDE; TITANIUM DIOXIDE; TALC

INDICATIONS AND USAGE

Uses: temporarily relieves minor aches and pains due to:•headache • minor pain of arthritis • the common cold • toothache • backache • menstrual cramps • muscular aches • temporarily reduces fever

If pregnant or breast-feeding, ask a health

professional before use. It is especially important not to

use Ibuprofen during the last 3 months of pregnancy

unless directed to do so by a doctor because it may

cause problems in the unborn

child or complications during delivery.

KEEP OUT OF REACH OF CHILDREN. In

case of overdose, get medical help or

contact a Poison Control Center right

away.

Warnings:

Allergy Alert: Ibuprofen may cause a severe allergic

reaction which may include:

• hives • shock • facial swelling • asthma (wheezing)

Alcohol Warning: If you consume 3 or more alcoholic

drinks every day, ask your doctor whether you should

take Ibuprofen or other pain relievers/ fever reducers.

Ibuprofen may cause stomach bleeding.

Do not use:

• if you have ever had an allergic reaction to any

other pain reliever/fever reducer

Ask a doctor before use if you have:

• stomach pain

• problems or serious side eects from taking

pain relievers or fever reducers

Ask a doctor or pharmacist before use if you are:

• under a doctor's care for any serious condition

• taking any other drug

• taking any other product that contains Ibuprofen,

or any other pain reliever/fever reducer

When using this product give with food or milk if

stomach upset occurs.

Stop use and ask a doctor if:

• an allergic reaction occurs. Seek medical help right

away • pain gets worse or lasts more than 10 days

• fever gets worse or lasts more than 3 days

• stomach pain or upset gets worse or lasts

• any new symptoms appear • redness or swelling is

present in the painful area

Directions:

• Do not take more than directed.

Adults and children 12 years and older

• Take 1 tablet every 4 to 6 hours while symptoms

• If pain or fever does not respond to 1 tablet, 2 tablets may be used.

Do not exceed 6 tablets in 24 hours, unless as directed by a doctor.

• The smallest effective dose should be used.

Children under 12 year

• Ask a doctor.

Inactive Ingredients:

carnauba wax, croscarmellose sodium,

hydroxypropyl methylcellulose,

microcrystalline cellulose,

polyethylene glycol, polysorbate 80,

povidone, pregelatinized starch, silicon

dioxide, sodium starch glycolate,

stearic acid and titanium dioxide.

ACTIVE INGREDIENT-IBUPROFEN 200 MG

PURPOSE

PAIN RELIEVER/FEVER REDUCER